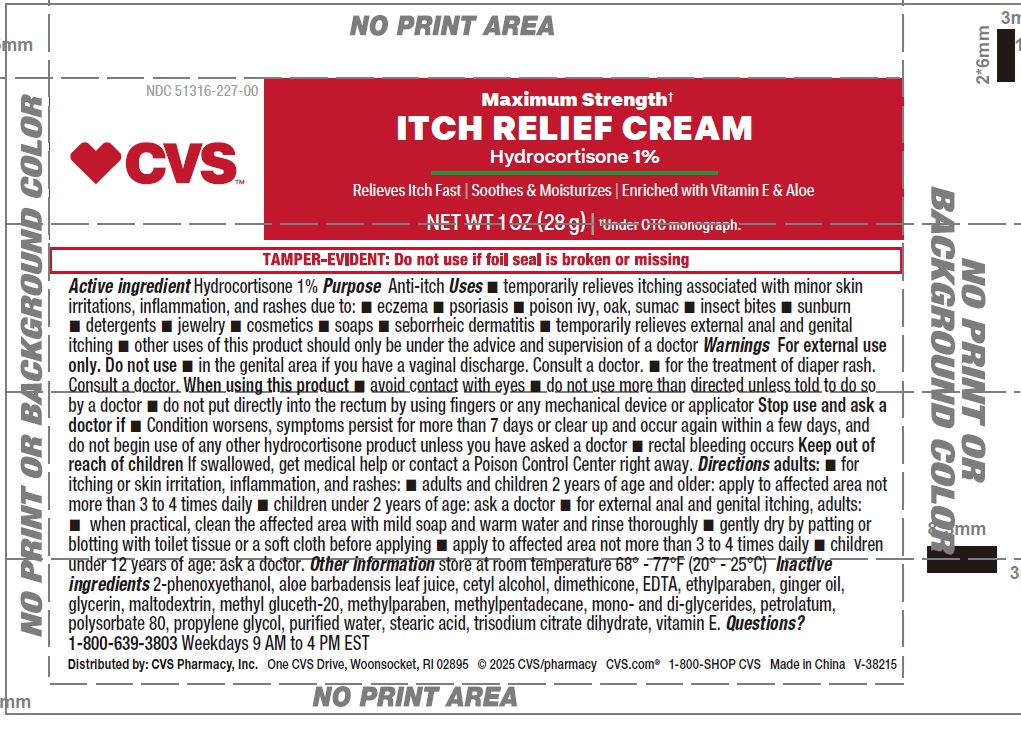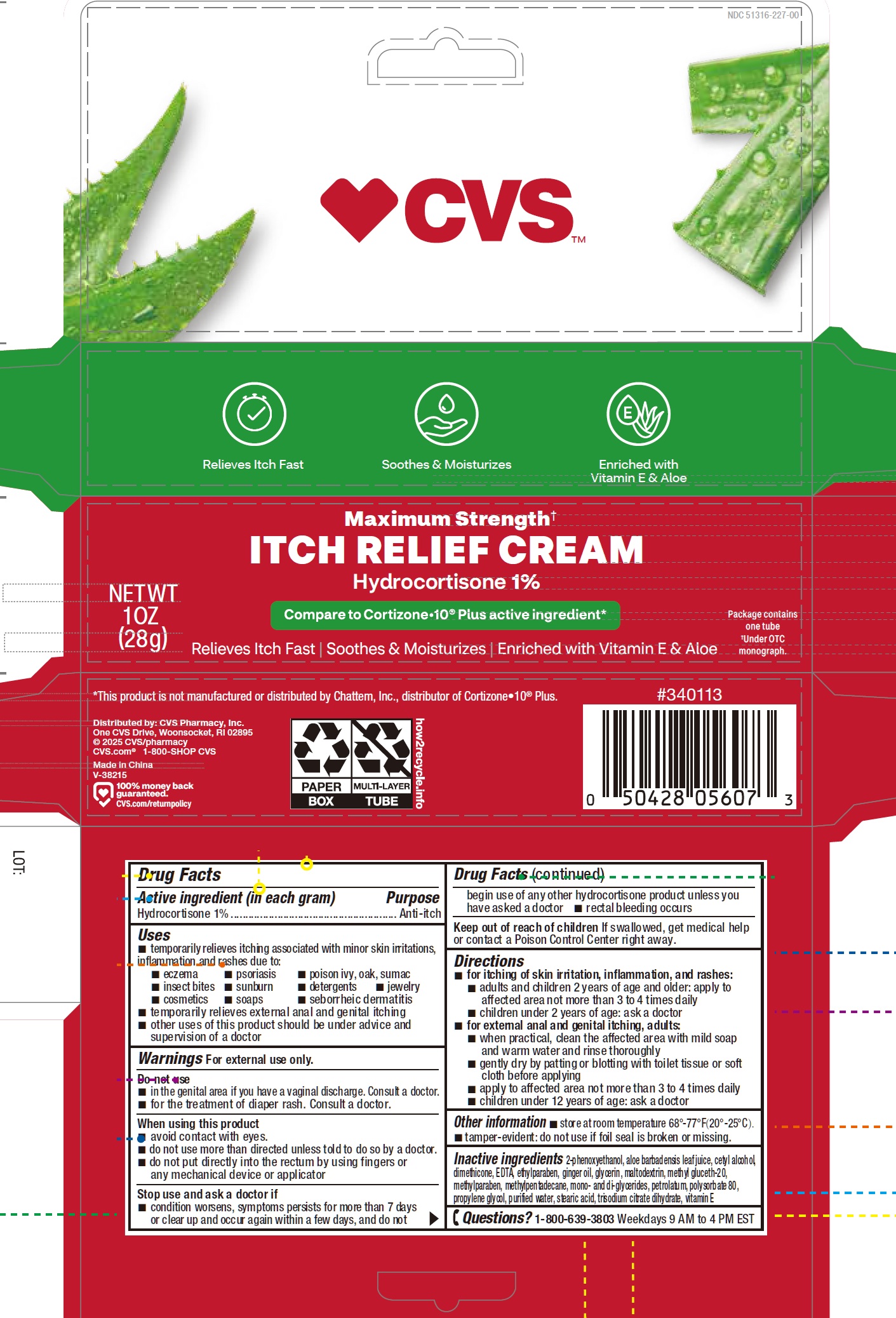 DRUG LABEL: HYDROCORTISONE
NDC: 51316-227 | Form: CREAM
Manufacturer: CVS PHARMACY, INC
Category: otc | Type: HUMAN OTC DRUG LABEL
Date: 20251007

ACTIVE INGREDIENTS: HYDROCORTISONE 10 mg/1 g
INACTIVE INGREDIENTS: PHENOXYETHANOL; ALOE VERA LEAF; CETYL ALCOHOL; DIMETHICONE; EDETIC ACID; ETHYLPARABEN; GINGER OIL; GLYCERIN; MALTODEXTRIN; METHYL GLUCETH-20; METHYLPARABEN; PETROLATUM; POLYSORBATE 80; PROPYLENE GLYCOL; WATER; STEARIC ACID; TRISODIUM CITRATE DIHYDRATE; .ALPHA.-TOCOPHEROL

HYDROCORTISONE 1% CREAM

Active ingredient (in each gram)

Hydrocortisone 1%

Purpose

Anti-itch

Uses

temporarily relieves itching associated with minor skin irritations, inflammation and rashes due to:

• eczema • psoriasis • poison ivy, oak, sumac • insect bites • sunburn • detergents • jewelry • cosmetics • soaps • seborrheic dermatitis • temporarily relieves external anal and genital itching • other uses of this product should be under advice and supervision of a doctor

Warnings

For external use only.

Do not use

- in the genital area if you have a vaginal discharge. Consult a doctor.
- for the treatment of diaper rash. Consult a doctor.

When using this product

- avoid contact with eyes.
- do not use more than directed unless told to do so by a doctor.
- do not put directly into the rectum by using fingers or any mechanical device or applicator

Stop use and ask a doctor if

- condition worsens, symptoms persists for more than 7 days or clear up and occur again within a few days, and do not begin use of any other hydrocortisone product unless you have asked a doctor
- rectal bleeding occurs

Keep out of reach of children

If swallowed, get medical help or contact a Poison Control Center right away.

Directions

- for itching of skin irritation, inflammation, and rashes:
- adults and children 2 years of age and older: apply to affected area not more than 3 to 4 times daily
- children under 2 years of age: ask a doctor
- for external anal and genital itching, adults:
- when practical, clean the affected area with mild soap and warm water and rinse thoroughly
- gently dry by patting or blotting with toilet tissue or soft cloth before applying
- apply to affected area not more than 3 to 4 times daily
- children under 12 years of age: ask a doctor

Other information

- store at room temperature 68°-77°F(20°-25°C).
- tamper-evident: do not use if foil seal is broken or missing.

Inactive ingredients

2-phenoxyethanol, aloe barbadensis leaf juice, cetyl alcohol, dimethicone, EDTA, ethylparaben, ginger oil, glycerin, glyceryl stearate, maltodextrin, methyl gluceth-20, methylparaben, methylpentadecane, petrolatum, polysorbate 80, propylene glycol, purified water, stearic acid, trisodium citrate dihydrate, vitamin E

Questions?

1-800-639-3803 Weekdays 9 AM to 4 PM EST